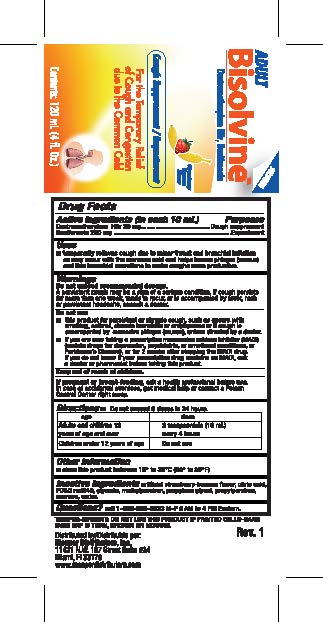 DRUG LABEL: Adult Bisolvine
NDC: 53145-323 | Form: LIQUID
Manufacturer: MENPER DISTRIBUTORS INC.
Category: otc | Type: HUMAN OTC DRUG LABEL
Date: 20250825

ACTIVE INGREDIENTS: DEXTROMETHORPHAN HYDROBROMIDE 20 mg/10 mL; GUAIFENESIN 200 mg/10 mL
INACTIVE INGREDIENTS: CITRIC ACID MONOHYDRATE; FD&C RED NO. 40; METHYLPARABEN; PROPYLENE GLYCOL; PROPYLPARABEN; WATER; SUCROSE

Adult Bisolvine

Active Ingredients (in each 10 mL) Purpose
Guaifenesin 200 mg ................................................ Expectorant
Dextromethorphan HBr 20mg.............................................. Cough Suppressant

Uses
* temporarily relieves cough due to minor throat and bronchial irritation as may occur with the common cold and helps loosen phlegm (mucus) and thin bronchial secretions to make coughs more productive.

Warnings: Do not exceed recommended dosage.
A persistent or chronic cough may be a sign of a serious condition. If cough persists for more than one week, tends to recur, or is accompanied by fever, rash, or persistent headache, consult a doctor.

Do not use:
* this product for persistent or chronic cough, such as occurs with smoking, asthma, or emphysema or if cough is accompanied by excessive phlegm (mucus), unless directed by a doctor.
* If you are now taking a prescription monoamine oxidase inhibitor (MAOI) (certain drugs for depression, psychiatric, or emotional conditions, or Parkinson's Disease), or for 2 weeks after stopping the MAOI drug. If you do not know if your prescription drug contains an MAOI, ask a doctor or pharmacist before taking this product.

Keep out of reach of children

PREGNANCY OR BREAST FEEDING

If pregnant or breast-feeding,ask a health professional before use. In case of accidental overdose, get medical help or contact a Poison Control Center right away.

Directions
* Do not exceed 6 doses in 24 hours
Age Dose
Adults and Children 2 teaspoonfuls (10 ml)
12 years of age and over every 4 hours
Children under 12 years of age Do not use

Other Information

- store this product between (15 to 30 C) (59 to 86 C)

Distributed by Menper Distributors, Inc.

6500 N.W. 35th Ave., Miami, Fl, 33147

www.menperdistributors.com

INACTIVE INGREDIENT

citric acid, fd&c red No.40, methyl paraben, propylene glycol, propylparaben, water, sucrose